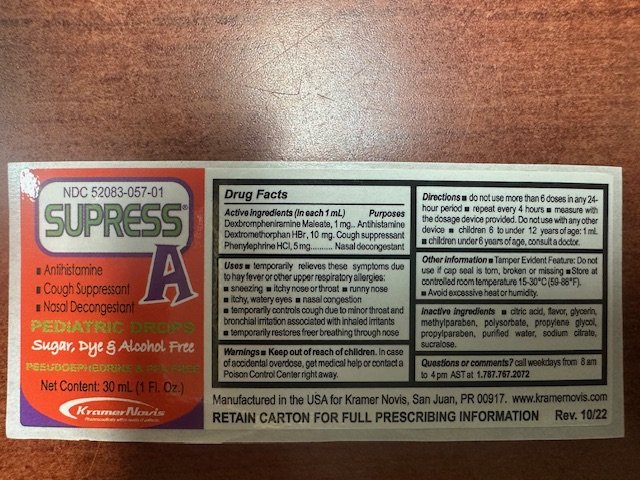 DRUG LABEL: Supres A
NDC: 65852-014 | Form: SYRUP
Manufacturer: Dextrum Laboratories, Inc
Category: otc | Type: HUMAN OTC DRUG LABEL
Date: 20251002

ACTIVE INGREDIENTS: DEXBROMPHENIRAMINE MALEATE 1 mg/1 mL; DEXTROMETHORPHAN HYDROBROMIDE 10 mg/1 mL; PHENYLEPHRINE HYDROCHLORIDE 5 mg/1 mL
INACTIVE INGREDIENTS: GLYCERIN; PROPYLPARABEN; PROPYLENE GLYCOL; SUCRALOSE; METHYLPARABEN; POLYSORBATE 20; WATER; SODIUM CITRATE; CITRIC ACID

Supress A

Active ingredient

Dexbrompheniramine Maleate, 1 mg

Dextromethorphan BBr, 10 mg

Phenylephrine HCL, 5 mg

Purpose section

Antihistaminie

Cough suppressant

Nasal descpngestant

Warnings Section:

Keep out of reach of childrens. In case of accidental overdose, get medical helpor contacta Poison Control Center right away.

Keep out of reach of childrens

In case of accidental overdose, get medical helpor contacta Poison Control Center right away.

Indication and usage section

Do not use more thab 6 doses in any 24-hour period, repeat ever 4 hour, measure with the dosage device provided.

Do not use with any other device.

Cildren under 6 years of age, consult a doctor

Inactive Ingredients

Citric acid, flavor, glycerin, methylparaben, polysorbate, propylene glycol, propylparaben, purified water, sodium citrate, sucralose

Question section

Question or comments call keekdays from 8 am to 4 pm AST at 1.787.767.2072

Dosage and administration section

Do not use more thab 6 doses in any 24-hour period, repeat ever 4 hour, measure with the dosage device provided.

Do not use with any other device.

Cildren under 6 years of age, consult a doctor

Principal Display Panel

NDC 52083-057-01

Supress A

Antistamine

cough Suppressant

Nasal descongestant

Pedriatic Drops

Sugar, Dye and alcohol free

Pseudoephedrine and PPA free

30ml (1FL OZ)

Kramer Novis